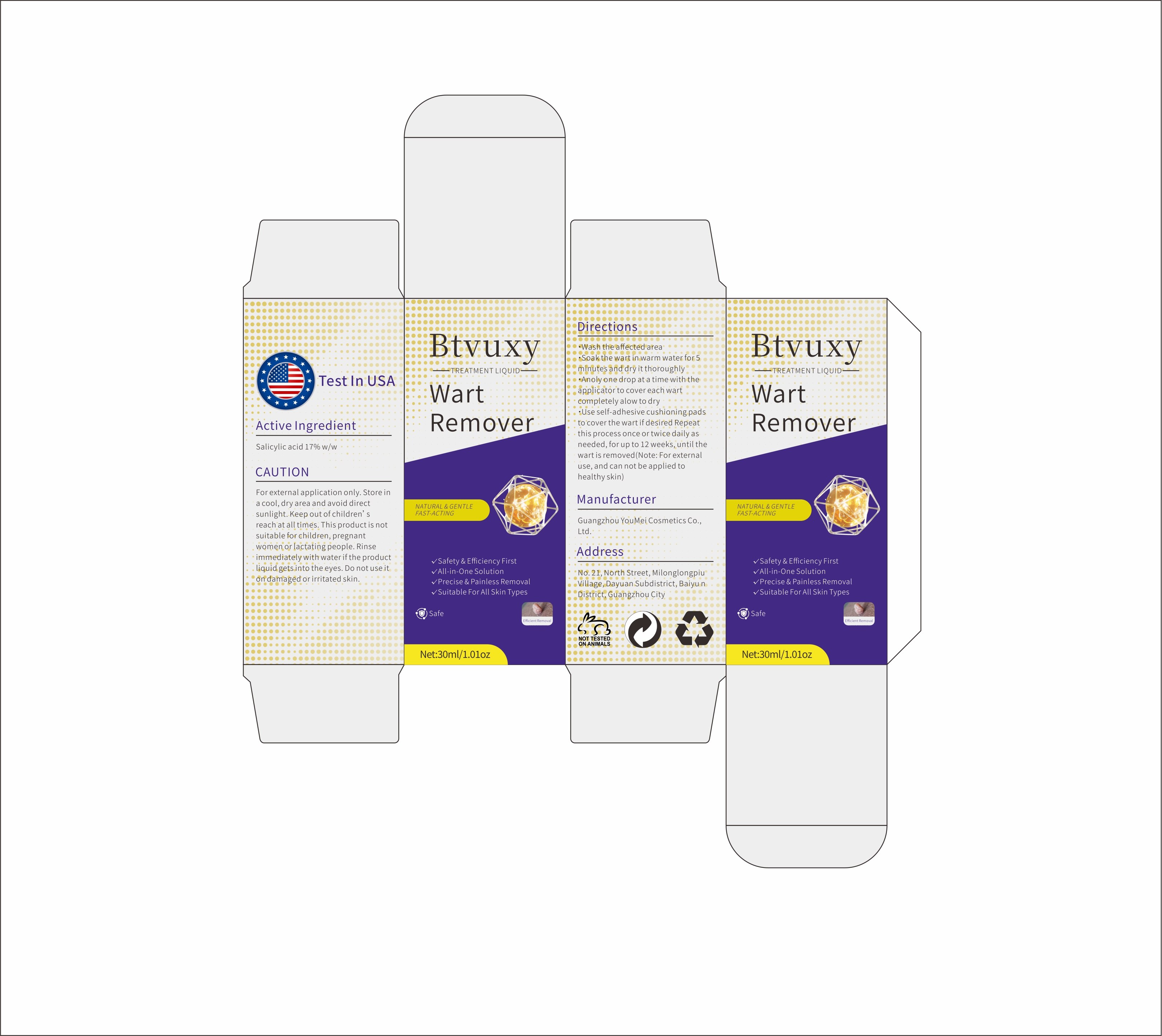 DRUG LABEL: Wart Remover Liquid
NDC: 74458-119 | Form: LIQUID
Manufacturer: Guangzhou Yilong Cosmetics.,Ltd
Category: otc | Type: HUMAN OTC DRUG LABEL
Date: 20260112

ACTIVE INGREDIENTS: SALICYLIC ACID 17 mg/100 mg
INACTIVE INGREDIENTS: WATER 50 mg/100 mg

Wart Remover Liquid

DESCRIPTION

Wash the affected area

Soak the wart or tag in warm water for 5 minutes and dry it thoroughly

Apply one drop at a time with the applicator to cover each wart or tag completely

Allow to dry, use self-adhesive cushioning pads to cover the wart or tag if desired

Repeat this process once or twice daily as needed, for up to 12 weeks, until the wart or tag is removed (Note: For external use, and can not be applied to healthy skin)

DOSAGE AND ADMINISTRATION

Repeat this procedure once or twice daily (as needed) for up to 12 weeks.

INDICATIONS AND USAGE

Wash the affected area

Soak the wart or tag in warm water for 5 minutes and dry it thoroughly

Apply one drop at a time with the applicator to cover each wart or tag completely

Allow to dry, use self-adhesive cushioning pads to cover the wart or tag if desired

Repeat this process once or twice daily as needed, for up to 12 weeks, until the wart or tag is removed (Note: For external use, and can not be applied to healthy skin)

WARNINGS

For external use only

Keep away from heat or flame

KEEP OUT OF REACH OF CHILDREN

Prevent children from swallowing.If swallowed, get medical help or contact a Poison Control Center right away.

PURPOSE

Wash the affected area

Soak the wart or tag in warm water for 5 minutes and dry it thoroughly

Apply one drop at a time with the applicator to cover each wart or tag completely

Allow to dry, use self-adhesive cushioning pads to cover the wart or tag if desired

Repeat this process once or twice daily as needed, for up to 12 weeks, until the wart or tag is removed (Note: For external use, and can not be applied to healthy skin)

INACTIVE INGREDIENT

Borneol, Glycerin,Podofilox,Polyethylene Glycol, Water, etc

PACKAGE LABEL

Wash the affected area

Soak the wart or tag in warm water for 5 minutes and dry it thoroughly

Apply one drop at a time with the applicator to cover each wart or tag completely

Allow to dry, use self-adhesive cushioning pads to cover the wart or tag if desired

Repeat this process once or twice daily as needed, for up to 12 weeks, until the wart or tag is removed (Note: For external use, and can not be applied to healthy skin)